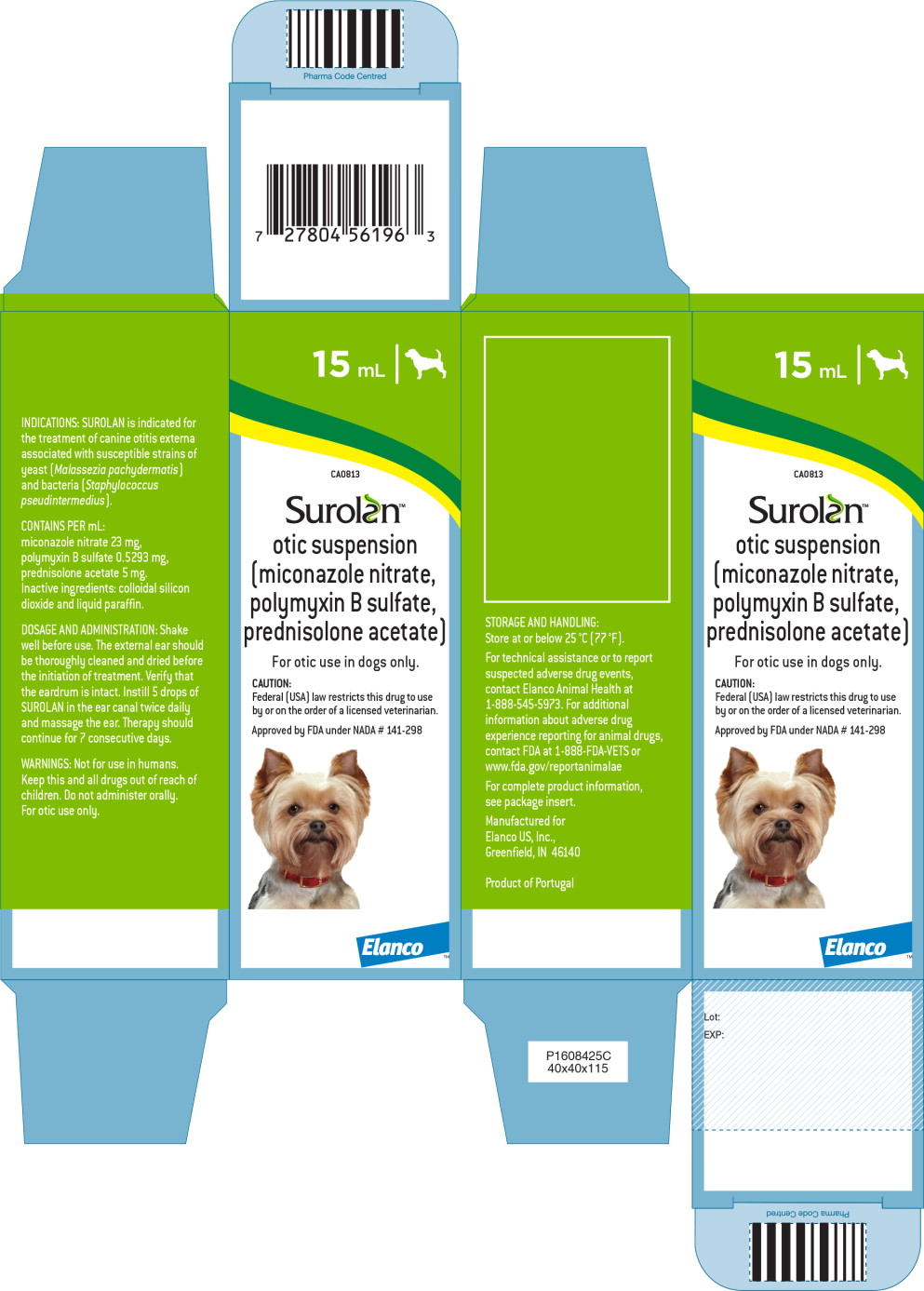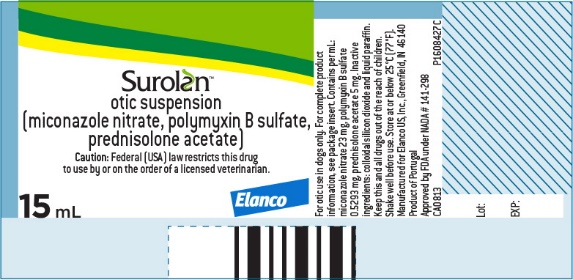 DRUG LABEL: Surolan
NDC: 58198-0813 | Form: SOLUTION/ DROPS
Manufacturer: Elanco US Inc.
Category: animal | Type: PRESCRIPTION ANIMAL DRUG LABEL
Date: 20221103

ACTIVE INGREDIENTS: MICONAZOLE NITRATE 23 mg/1 mL; POLYMYXIN B SULFATE .05293 mg/1 mL; PREDNISOLONE ACETATE 5 mg/1 mL

Surolan™
Rx otic suspension
(miconazole nitrate, polymyxin B sulfate, prednisolone acetate)

Antifungal, antibacterial and anti-inflammatory

For otic use in dogs only

CAUTION

Federal (USA) law restricts this drug to use by or on the order of a licensed veterinarian.

DESCRIPTION

SUROLAN contains 23 mg/mL miconazole nitrate, 0.5293 mg/mL polymyxin B sulfate and 5 mg/mL prednisolone acetate. Inactive ingredients are colloidal silicon dioxide and liquid paraffin.

INDICATIONS

SUROLAN is indicated for the treatment of canine otitis externa associated with susceptible strains of yeast (Malassezia pachydermatis) and bacteria (Staphylococcus pseudintermedius).

DOSAGE AND ADMINISTRATION

Shake well before use.

The external ear should be thoroughly cleaned and dried before the initiation of treatment. Verify that the eardrum is intact. Instill 5 drops of SUROLAN in the ear canal twice daily and massage the ear. Therapy should continue for 7 consecutive days.

CONTRAINDICATIONS

SUROLAN is contraindicated in dogs with suspected or known hypersensitivity to miconazole nitrate, polymyxin B sulfate, or prednisolone acetate.

Do not use in dogs with known perforated tympanum. Do not use with drugs known to induce ototoxicity.

WARNINGS

Not for use in humans. Keep this and all drugs out of reach of children.

ANIMAL WARNINGS

Do not administer orally.

For otic use only.

PRECAUTIONS

Before instilling any medication into the ear, examine the external ear canal thoroughly to be certain the tympanic membranes are not ruptured.

If overgrowth of non-susceptible bacteria or fungi occurs, treatment should be discontinued and appropriate therapy instituted.

Long-term use of topical otic corticosteroids has been associated with adrenocortical suppression and iatrogenic hypoadrenalcorticism in dogs.

The safe use of SUROLAN in dogs used for breeding purposes, during pregnancy, or in lactating bitches, has not been evaluated.

ADVERSE REACTIONS

In the field study, 161 dogs treated with SUROLAN were included in the safety database. Two dogs experienced reduced hearing at the end of treatment; on follow-up one dog had normal hearing capacity while the other case was lost for follow-up. The owner of another dog reported that on day 4 of treatment, build-up of the medication decreased the dog's hearing. At the end of treatment, this dog had normal hearing as assessed by the investigator. Residue build-up was reported in 1 dog and pain upon drug application in another dog.

A total of 161 dogs treated with the active control was included in the safety database and adverse reactions were reported in 8 dogs treated with the active control. One dog experienced reduced hearing at the end of treatment. Residue build-up was noted in 1 dog. Four dogs vomited during treatment, 1 dog showed red pustules on the pinna and head shaking was observed in another dog.

Foreign market experience: the following adverse events were reported voluntarily during post-approval use of the product in foreign markets: deafness, reduced hearing, topical hypersensitivity reactions and red blisters on pinna.

For a copy of the Safety Data Sheet (SDS), for technical assistance or to report a suspected adverse drug reaction, contact Elanco Animal Health at 1-888-545-5973. Alternatively, suspected adverse drug reactions may be reported to FDA at 1-888-FDA-VETS or www.fda.gov/reportanimalae

PHARMACOLOGY

By virtue of its 3 active ingredients, SUROLAN has antibacterial, antifungal, and anti-inflammatory activity. Polymyxin B sulfate is a broad-spectrum polypeptide antibiotic with activity against both Gram-positive and Gram-negative species. Miconazole nitrate is a synthetic imidazole derivative with antifungal activity and antibacterial activity against Gram-positive bacteria. Moreover, synergistic effects between miconazole nitrate and polymyxin B sulfate have been demonstrated in an in vitro study(1). Prednisolone acetate is a glucocorticoid with anti-inflammatory activity. A study performed using an experimentally-induced model of ear inflammation in mice demonstrated the effectiveness of prednisolone acetate in treating ear inflammation either alone or in combination with the other active ingredients of SUROLAN(2).

MICROBIOLOGY

The compatibility and additive effect of each of the components in SUROLAN was demonstrated in a component effectiveness and non-interference study. An in vitro study of organisms collected from clinical cases of otitis externa at a veterinary teaching hospital and from dogs enrolled in the clinical effectiveness study for SUROLAN determined that polymyxin B sulfate and miconazole nitrate inhibit the growth of bacteria and yeast commonly associated with canine otitis externa. Furthermore, a synergistic effect of the two antimicrobials was demonstrated. The addition of prednisolone acetate to the combination did not impair antimicrobial activity to any clinically-significant extent.

ANIMAL SAFETY

The following adverse reactions were reported in a study when SUROLAN was administered at 1X, 3X and 5X for 42 consecutive days (6 times the recommended treatment duration) in laboratory Beagles: hypersensitivity reactions which included mild erythema and hyperemia, painful and sensitive ear canals on examination, changes in hematology, clinical chemistry and urinalysis values consistent with the systemic absorption of topical corticosteroids, and veterinary observations of pale ear canals.

EFFECTIVENESS

Of 337 dogs enrolled in the field study, 176 dogs were included in the effectiveness database; 91 were treated with SUROLAN and 85 were treated with an FDA-approved active control. Clinical evaluations of otitis externa included pain/discomfort, swelling, redness, and exudate. A non-inferiority evaluation was used to compare SUROLAN with the active control with respect to each clinical sign of otitis externa and overall clinical improvement. SUROLAN was determined to be non-inferior to treatment with the active control for otitis externa. Malassezia pachydermatis and Staphylococcus pseudintermedius were identified pre-treatment in at least 10 cases that were clinically responsive to SUROLAN.

Table 1. Mean Percentage of Improvement in Clinical Signs of Otitis Externa
Clinical sign | SUROLAN N=91 | Active control N=85
Pain/discomfort | 94.4% | 91.7%
Swelling | 89.1% | 90.5%
Redness | 91.2% | 86.1%
Exudate | 83.1% | 82.1%
Overall | 96.7% | 95.2%

HOW SUPPLIED

SUROLAN is available in 15 mL and 30 mL plastic dispensing bottles with applicator tip for otic use.

STORAGE AND HANDLING

Store at or below 25 °C (77 °F).

Approved by FDA under NADA # 141-298

Manufactured for Elanco US, Inc.,
Greenfield, IN 46140

Product of Portugal

Surolan, Elanco and the diagonal bar logo are trademarks of Elanco or its affiliates.
© 2021 Elanco or its affiliates

CA081315HAM
CA081330HAM

March 2021

REFERENCES

1. Pietschmann S. et al. (2009)
  Synergistic effects of miconazole and polymyxin B on microbial pathogens.
  Veterinary Research Communications 33(6), 489-505
2. Bolinder A. et al. (2006)
  In vivo efficacy study of the anti-inflammatory properties of Surolan
  The Canadian Journal of Veterinary Research 70, 234-236

ElancoTM

Principal Display Panel – 15 mL Carton Label

15 mL

CA0813

Surolan™

otic suspension
(miconazole nitrate,
polymyxin B sulfate,
prednisolone acetate)

For otic use in dogs only.

CAUTION:

Federal (USA) law restricts this drug to use by or on the order of a licensed veterinarian.

Approved by FDA under NADA # 141-298

ElancoTM

Principal Display Panel – 15 mL Bottle Label

Surolan™

otic suspension
(miconazole nitrate, polymyxin B sulfate,
prednisolone acetate)

Caution: Federal (USA) law restricts this drug
to use by or on the order of a licensed veterinarian.

15 mL

Elanco